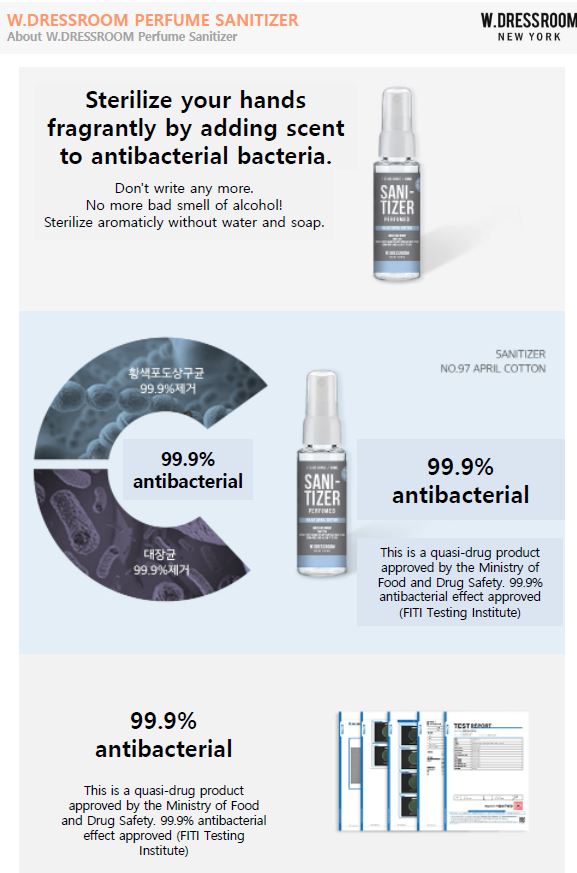 DRUG LABEL: W.Dressroom Perfumed Sanitizer Peach Blossom
NDC: 80080-0001 | Form: LIQUID
Manufacturer: Trend-I Inc
Category: otc | Type: HUMAN OTC DRUG LABEL
Date: 20200824

ACTIVE INGREDIENTS: ALCOHOL 62 mL/100 mL
INACTIVE INGREDIENTS: GLYCERIN; ALLANTOIN; WATER

ACTIVE INGREDIENT

alcohol

INACTIVE INGREDIENT

glycerin, allantoin, water, butylene glycol, niacinamide, DL-panthenol, xylitol, glycine, aloe vera leafr, acorus calamus extract, panax ginseng extract, cortex mori extract, paeonia lactiflora root extract, swertia pseudochinensis extract, citrus unshiu peel extract, fragrance

PURPOSE

hand sanitizer

keep out of reach of the children

INDICATIONS AND USAGE

When you wish to sanitize your hands, and after you wash your hands

WARNINGS

For external use only. Flammable. Keep away from heat or flame.

Do not use

- in children less than 2 months of age
- on open skin wounds

When using this product keep out of eyes, ears, and mouth. In case of contact with eyes, rinse thoroughly with water.

Stop use and ask a doctor if irritation or rash occurs. These may be signs of a serious condition.

Keep out of reach of children. If swallowed, get medical help or contact a Poison Control Center right away.

DOSAGE AND ADMINISTRATION

for external use only